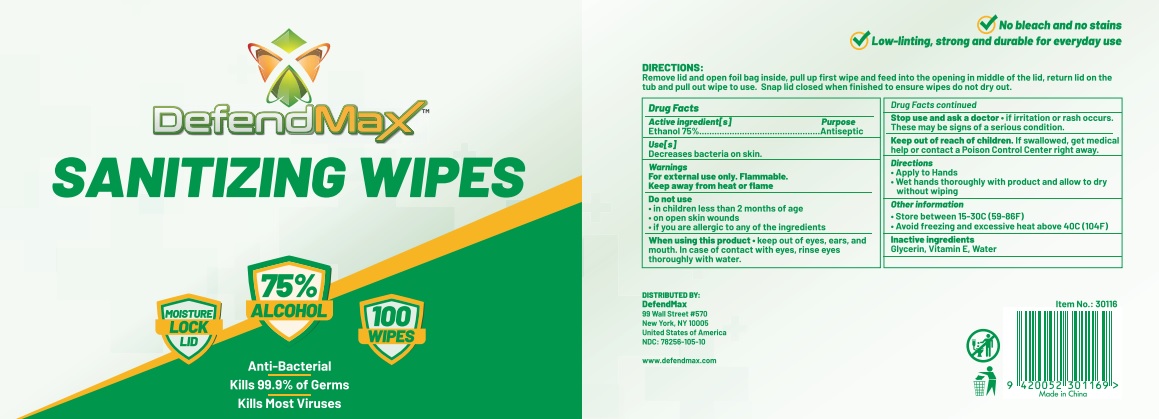 DRUG LABEL: DefendMax Sanitizing Wipes
NDC: 78256-105 | Form: CLOTH
Manufacturer: Etailer Limited
Category: otc | Type: HUMAN OTC DRUG LABEL
Date: 20200930

ACTIVE INGREDIENTS: ALCOHOL 75 g/100 g
INACTIVE INGREDIENTS: .ALPHA.-TOCOPHEROL; GLYCERIN; WATER

DefendMax Sanitizing Wipes (cloth) NDC: 78256-105-10

Active Ingredient(s)

Ethanol 75% v/v

Purpose

Antiseptic

Use(s)

Decreases bacteria on skin.

Warnings

For external use only. Flammable. Keep away from heat or flame

Do not use

- in children less than 2 months of age
- on open skin wounds
- if you are allergic to any of the ingredients

When using this product keep out of eyes, ears, and mouth. In case of contact with eyes, rinse eyes thoroughly with water.

Stop use and ask a doctor if irritation or rash occurs. These may be signs of a serious condition.

Keep out of reach of children. If swallowed, get medical help or contact a Poison Control Center right away.

Directions

- Apply to Hands
- Wet hands thoroughly with product and allow to dry without wiping.

Other information

- Store between 15-30C (59-86F)
- Avoid freezing and excessive heat above 40C (104F)

Inactive ingredients

Glycerin, Vitamin E, Water

Package Label - Principal Display Panel

DISTRIBUTED BY:

DefendMax

99 Wall Street #570

New York, NY 10005

United States of America

DefendMax Sanatizing Wipes (cloth - 100 ct) NDC: 78256-105-10